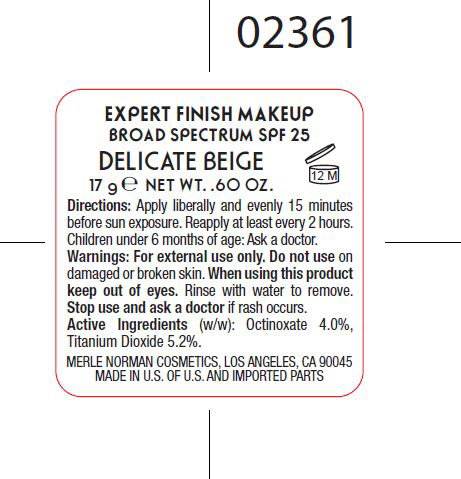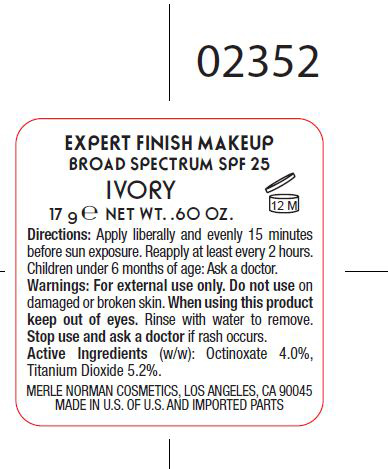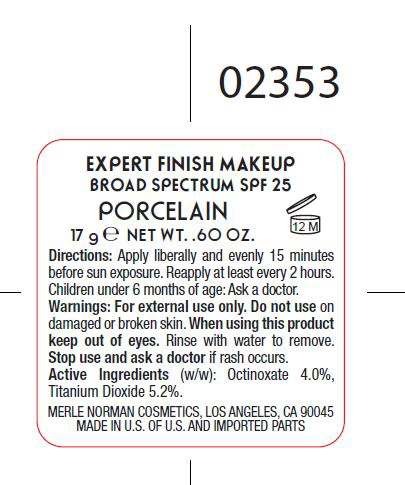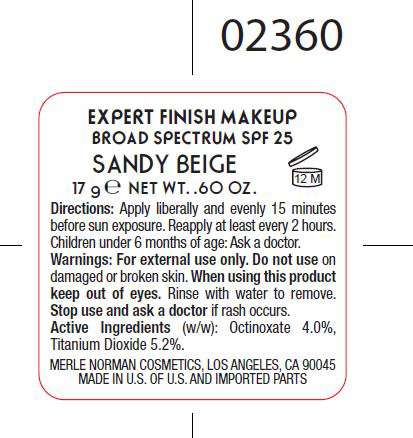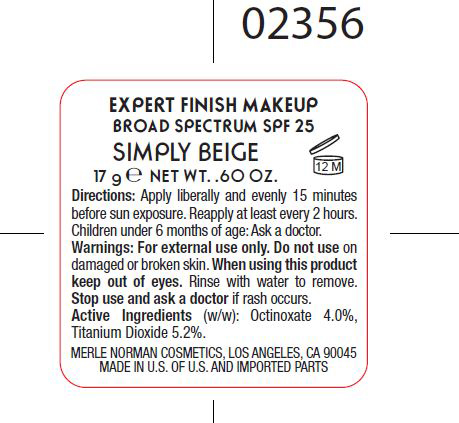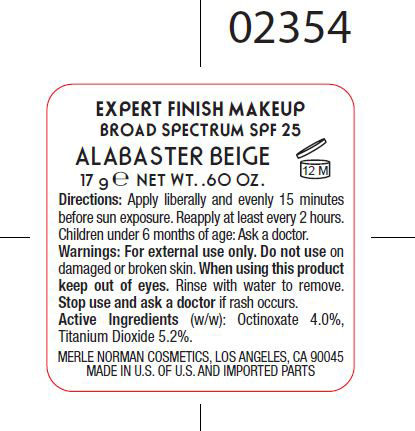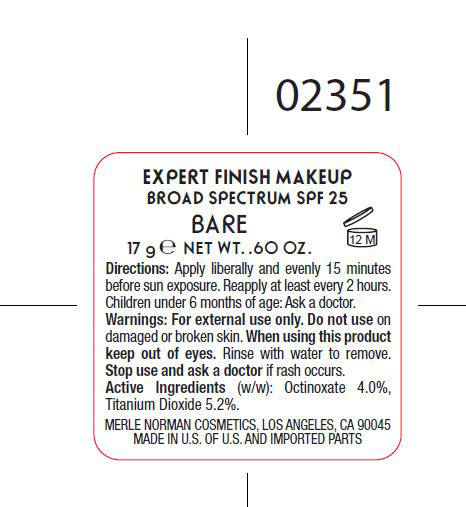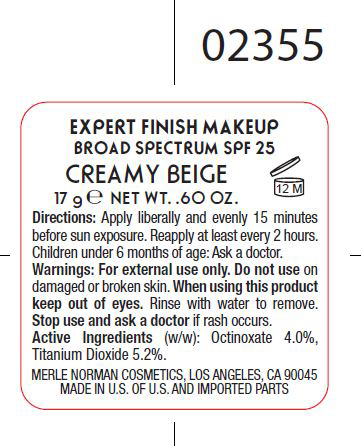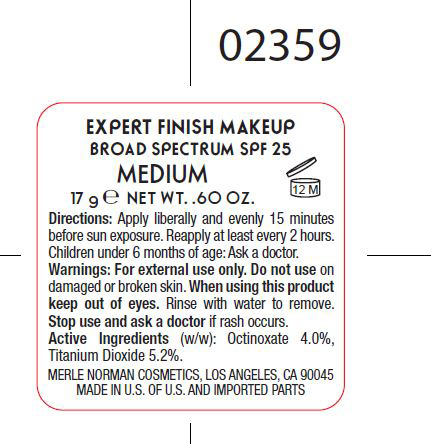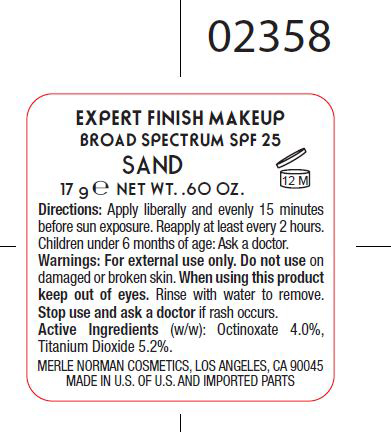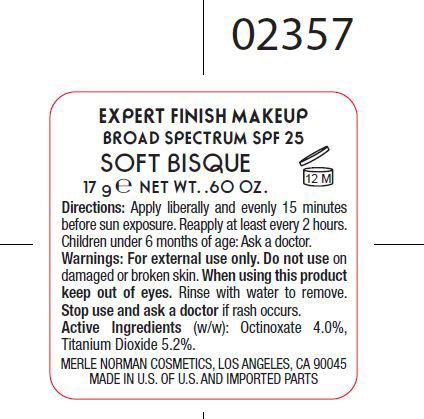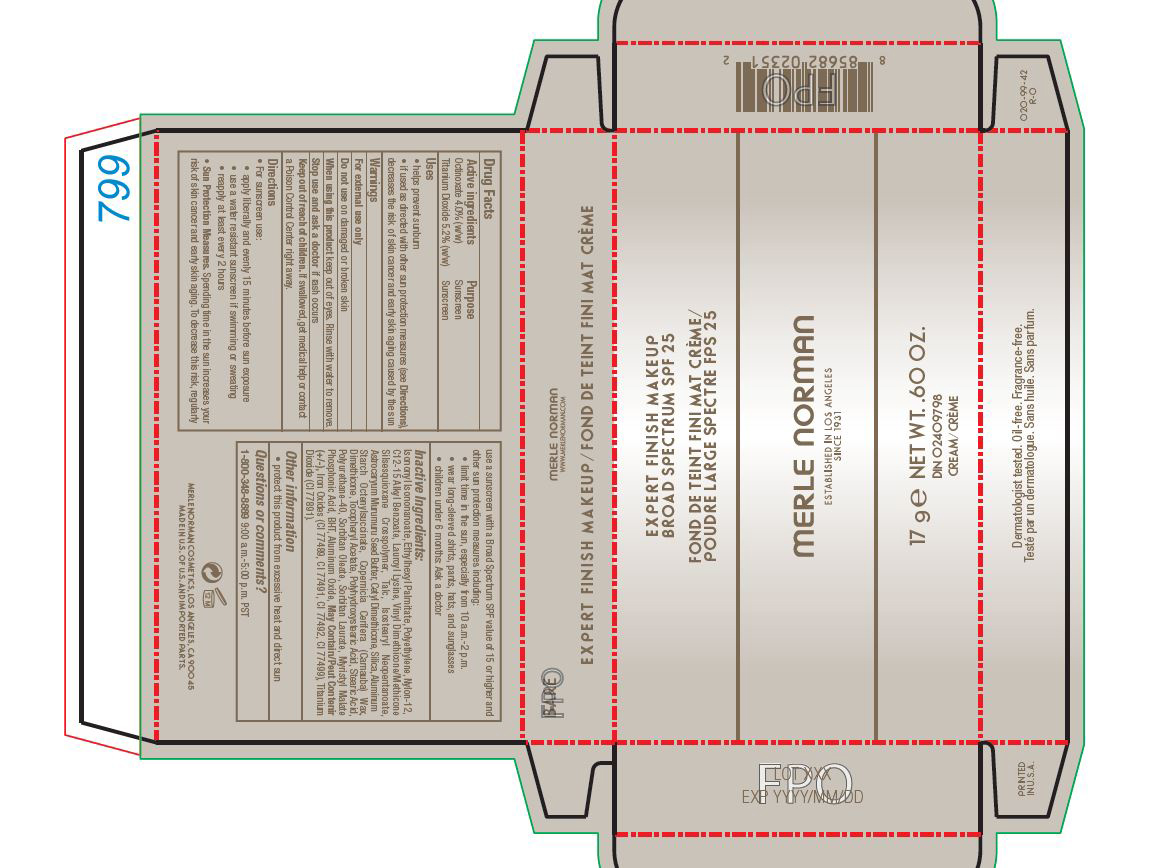 DRUG LABEL: Bare Expert Finish Makeup Broad Spectrum SPF 25
NDC: 57627-157 | Form: CREAM
Manufacturer: Merle Norman Cosmetics, Inc
Category: otc | Type: HUMAN OTC DRUG LABEL
Date: 20251118

ACTIVE INGREDIENTS: OCTINOXATE 4 g/100 g; TITANIUM DIOXIDE 5.2 g/100 g
INACTIVE INGREDIENTS: ISONONYL ISONONANOATE; ETHYLHEXYL PALMITATE; HIGH DENSITY POLYETHYLENE; NYLON-12; ALKYL (C12-15) BENZOATE; LAUROYL LYSINE; TALC; ISOSTEARYL NEOPENTANOATE; ASTROCARYUM MURUMURU SEED BUTTER; CETYL DIMETHICONE 25; SILICON DIOXIDE; ALUMINUM STARCH OCTENYLSUCCINATE; CARNAUBA WAX; DIMETHICONE; .ALPHA.-TOCOPHEROL ACETATE; POLYHYDROXYSTEARIC ACID (2300 MW); STEARIC ACID; SORBITAN MONOOLEATE; SORBITAN MONOLAURATE; PHOSPHONIC ACID; BUTYLATED HYDROXYTOLUENE; ALUMINUM OXIDE; FERRIC OXIDE RED

Expert Finish Makeup SPF 25

Active Ingredients Purpose

Octinoxate 4.0% Sunscreen

Titanium Dioxide 5.2% Sunscreen

Uses

- helps prevent sunburn

- if used as directed with other sun protection measures (see Directions), decreases the risk of skin cancer and early skin aging caused by the sun

Keep out of reach of children. If swallowed, get medical help or contact a Poison Control Center right away

Stop use and ask a doctor if rash occurs

Warnings

For external use only

Do not use on damaged or broken skin

When using this product, keep out of eyes. Rinse with water to remove.

Directions

For sunscreen use

apply liberally and evenly 15 minutes before sun exposure

use a water resistant sunscreen if swimming or sweating

reapply at least every 2 hours

Sun Protection Measures. Spending time in the sun increases your risk of skin cancer and early skin aging. To decrease this risk, regularly use a sunscreen with a broad spectrum SPF value of 15 or higher and other sun protection measures including:

limit time in the sun, especially from 10 a.m. -2 p.m.

wear long sleeve shirts, pants, hats, and sunglasses

children under 6 months: Ask a doctor

Inactive Ingredients

Isononyl Isononanoate, Ethylhexyl Palmitate, Polyethylene, Nylon-12, C12-15 Alkyl Benzoate, Lauroyl Lysine, Vinyl Dimethicone/Methicone Silsesquioxane Crosspolymer, Talc, Isostearyl Neopentanoate, Astrocaryum Murumuru Seed Butter, Cetyl Dimethicone, Silica, Aluminum Starch Octenylsuccinate, Copernicia Cerifera (Carnauba) Wax, Dimethicone, Tocopheryl Acetate, Polyhydroxystearic Acid, Stearic Acid, Polyurethane-40, Sorbitan Oleate, Sorbitan Laurate, Myristyl Malate Phosphonic Acid, BHT Aluminum Oxide, May Contain, Iron Oxides, Titanium Dioxide

PACKAGE LABEL

Expert Finish Makeup Broad Spectrum SPF 25

Merle Norman

17 g Net Wt. .60 Oz